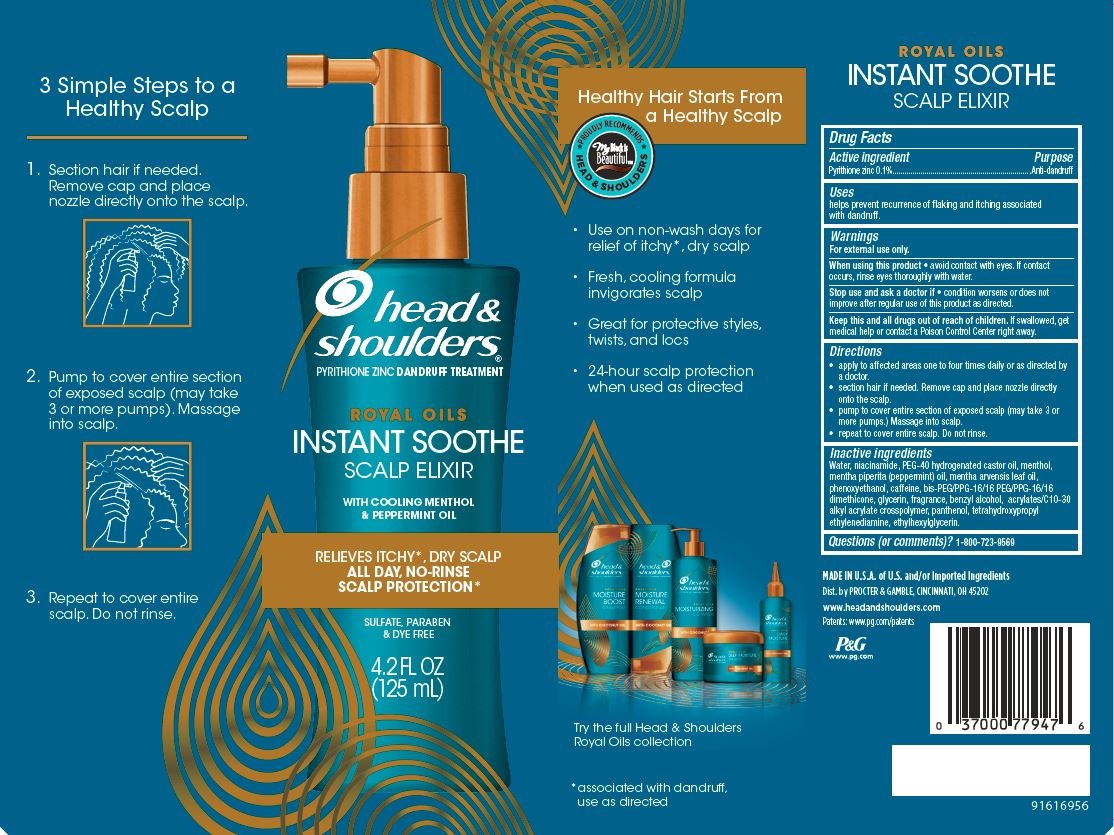 DRUG LABEL: Head and Shoulders Royal Oils Instant Soothe Scalp
NDC: 69423-309 | Form: LOTION
Manufacturer: The Procter & Gamble Manufacturing Company
Category: otc | Type: HUMAN OTC DRUG LABEL
Date: 20251218

ACTIVE INGREDIENTS: PYRITHIONE ZINC 0.1 g/100 mL
INACTIVE INGREDIENTS: CARBOMER COPOLYMER TYPE A; NIACINAMIDE; WATER; POLYOXYL 40 HYDROGENATED CASTOR OIL; MENTHOL, UNSPECIFIED FORM; GLYCERIN; PHENOXYETHANOL; BENZYL ALCOHOL; PEPPERMINT OIL; MENTHA ARVENSIS LEAF OIL; CAFFEINE; BIS-PEG/PPG-16/16 PEG/PPG-16/16 DIMETHICONE; COCONUT OIL; PANTHENOL; EDETOL; ETHYLHEXYLGLYCERIN

Head and Shoulders® Royal Oils Instant Soothe Scalp Elixir

Drug Facts

Active ingredient

Pyrithione zinc 0.1%

Purpose

Anti-dandruff

Uses

helps prevent recurrence of flaking and itching associated with dandruff.

Warnings

For external use only.

When using this product

- avoid contact with eyes. If contact occurs, rinse eyes thoroughly with water.

Stop use and ask a doctor if

- condition worsens or does not improve after regular use of this product as directed.

KEEP OUT OF REACH OF CHILDREN

Keep this and all drugs out of reach of children. If swallowed, get medical help or contact a Poison Control Center right away.

Directions

• apply to affected areas one to four times daily or as directed by

a doctor.

• section hair if needed. Remove cap and place nozzle directly

onto the scalp.

• pump to cover entire section of exposed scalp (may take 3 or

more pumps.) Massage into scalp.

• repeat to cover entire scalp. Do not rinse.

Inactive ingredients

Water, niacinamide, PEG-40 hydrogenated castor oil, menthol, mentha piperita (peppermint) oil, mentha arvensis leaf oil, phenoxyethanol, caffeine, bis-PEG/PPG-16/16 PEG/PPG-16/16 dimethicone, glycerin, fragrance, benzyl alcohol, acrylates/C10-30 alkyl acrylate crosspolymer, panthenol, tetrahydroxypropyl ethylenediamine, ethylhexylglycerin.

Questions (or comments)?

1-800-723-9569

Dist. by PROCTER & GAMBLE,
CINCINNATI, OH 45202

PRINCIPAL DISPLAY PANEL - 125 mL Carton

head &
shoulders®
pyrithione zinc dandruff treatment

ROYAL OILS

INSTANT SOOTHE

SCALP ELIXIR

with COOLING MENTHOL

& PEPPERMINT OIL

RELIEVES ITCHY*, DRY SCALP

ALL DAY, NO-RINSE

SCALP PROTECTION*

SULFATE, PARABEN &

DYE FREE

4.2 FL OZ
(125 mL)